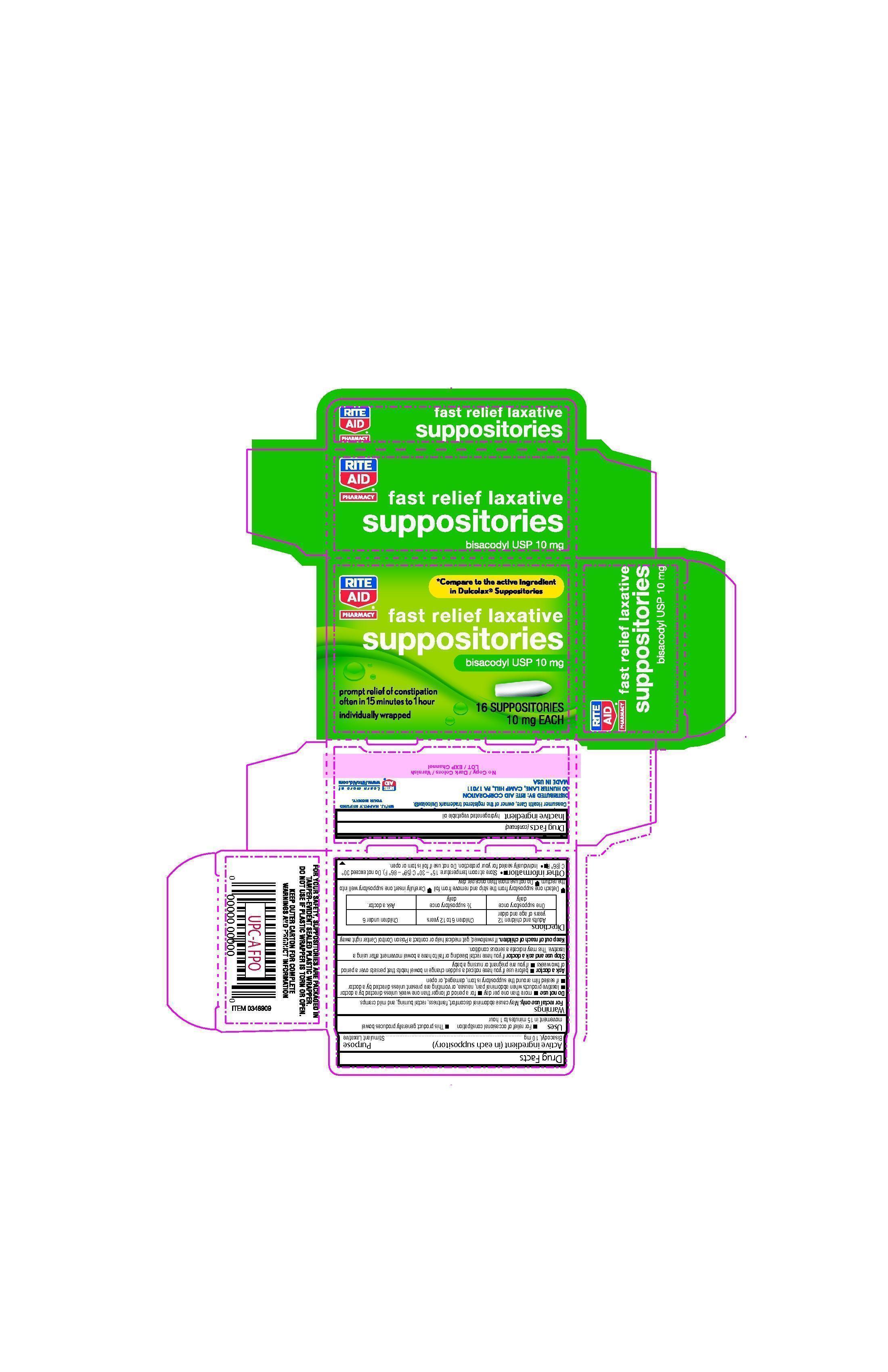 DRUG LABEL: Rite Aid fast relief laxative
NDC: 11822-4601 | Form: SUPPOSITORY
Manufacturer: Rite Aid Pharmacy
Category: otc | Type: HUMAN OTC DRUG LABEL
Date: 20211216

ACTIVE INGREDIENTS: BISACODYL 10 mg/2000 mg
INACTIVE INGREDIENTS: PALM KERNEL OIL 1990 mg/2000 mg

RITE AID® Fast Relief Laxative Suppositories 16 ct

Active Ingredient (in each Suppository) Purpose

Bisacodyl, 10 mg...................................Stimulant Laxative

Uses

Uses - For relief of occasional constipation -This product generally produces bowel movement in 15 minutes to 1 hour

Warnings

For rectal use only. May cause abdominal discomfort, faintness, rectal burning, and mild cramps.

Ask a doctor -before use if you have noticed a sudden change in bowel habits that periss over a period of two weeks -if you are pregnant or nursing a baby

Stop use and ask a doctor if you have rectal bleeding or fail to have bowel movement after using a laxative. This may indicate a serious condition.

Keep out of reach of children. If swallowed, get medical help or contact a Poison Control Center right away.

Directions

Adults and children 12 years of age and older Children 6 to 12 years Children under 6

One suppository once daily 1/2 suppository once daily Ask doctor

-Detach one suppository from the strip and remove from foil - Carefully insert one suppositry well into the rectum

-Do not use more than once per day

Other information

Other information - Store at room temperature: 15o - 30oC (59o - 86oF). Do not exceed 30oC (86oF) - Individually sealed for your protection. Do not use if foil is torn or open

Inactive ingredient

Inactive ingredient hydrogenated vegetable oil

Purpose

Active Ingredient (in each Suppository) Purpose
Bisacodyl, 10 mg...................................Stimulant Laxative

Do not use -more than one per day -for a period oflonger than one week unless directed by a doctor -laxative products when abdominal pain, nausea, or vomiting are present unless directed by a doctor -if sealed film around the suppository is torn, damaged, or open